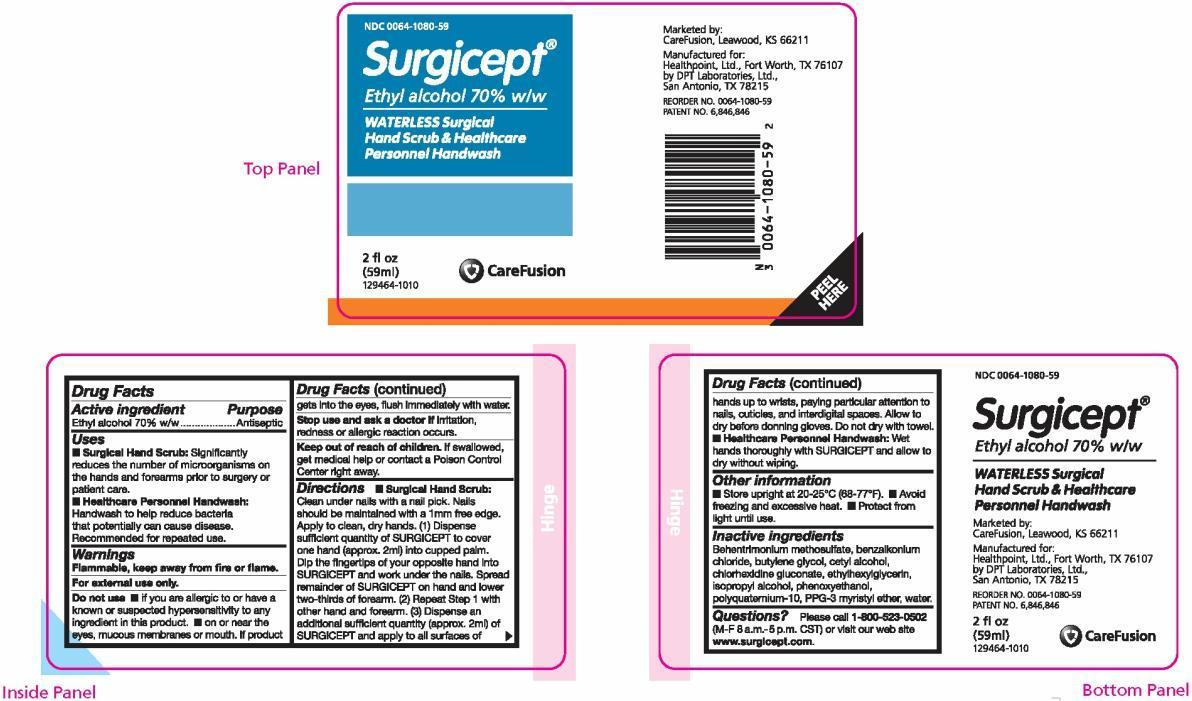 DRUG LABEL: SURGICEPT

NDC: 0064-1080 | Form: SOLUTION
Manufacturer: HEALTHPOINT, LTD
Category: otc | Type: HUMAN OTC DRUG LABEL
Date: 20170911

ACTIVE INGREDIENTS: ALCOHOL 0.75 mL/1 mL
INACTIVE INGREDIENTS: BEHENTRIMONIUM METHOSULFATE; BENZALKONIUM CHLORIDE; BUTYLENE GLYCOL; CETYL ALCOHOL; CHLORHEXIDINE GLUCONATE; ETHYLHEXYLGLYCERIN; ISOPROPYL ALCOHOL; PHENOXYETHANOL; POLYQUATERNIUM-10 (400 CPS AT 2%); WATER

SURGICEPT WATERLESS Surgical Hand Scrub & Healthcare Personnel Handwash – alcohol solution
CareFusion

Drug Facts

Active ingredient

Ethyl alcohol 70% w/w

Purpose

Antiseptic

Uses

- Surgical Hand Scrub: Significantly reduces the number of microorganisms on the hands and forearms prior to surgery or patient care.
- Healthcare Personnel Handwash: Handwash to help reduce bacteria that potentially can cause disease. Recommended for repeated use.

Warnings

- Flammable, keep away from fire or flame.
- For external use only.
- Do not use
  - if you are allergic to or have a known or suspected hypersensitivity to any ingredient in this product.
  - on or near the eyes, mucous membranes or mouth. If product gets into the eyes, flush immediately with water.
- Stop use and ask a doctor if irritation, redness or allergic reaction occurs.
- Keep out of reach of children. If swallowed, get medical help or contact a Poison Control Center right away.

Directions

- Surgical Hand Scrub: Clean under nails with a nail pick. Nails should be maintained with a 1mm free edge. Apply to clean, dry hands. (1) Dispense sufficient quantity of SURGICEPT to cover one hand (approx. 2ml) into cupped palm. Dip the fingertips of your opposite hand into SURGICEPT and work under the nails. Spread remainder of SURGICEPT on hand and lower two-thirds of forearm. (2) Repeat Step 1 with other hand and forearm. (3) Dispense an additional sufficient quantity (approx. 2ml) of SURGICEPT and apply to all surfaces of hands up to wrists, paying particular attention to nails, cuticles, and interdigital spaces. Allow to dry before donning gloves. Do not dry with a towel.
- Healthcare Personnel Handwash: Wet hands thoroughly with SURGICEPT and allow to dry without wiping.

Other information

- Store upright at 20-25°C (68-77°F)
- Avoid freezing and excessive heat.
- Protect from light until use.

Inactive ingredients

Behentrimonium methosulfate, benzalkonium chloride, butylene glycol, cetyl alcohol, chlorhexidine gluconate, ethylhexylglycerin, isopropyl alcohol, phenoxyethanol, polyquaternium-10, PPG-3 myristyl ether, water.

Questions?

Please call 1-800-523-0502 (M-F 8 a.m.-5 p.m. CST) or visit our web site www.surgicept.com.

PRINCIPAL DISPLAY PANEL

NDC 0064-1080-59

Surgicept®

Ethyl alcohol 70% w/w

WATERLESS Surgical Hand Scrub & Healthcare Personnel Handwash

2 fl oz (59 ml)
129464-1010

Marketed by:
CareFusion, Leawood, KS 66211

Manufactured for:
Healthpoint, Ltd., Fort Worth, TX 76107
by DPT Laboratories, Ltd., San Antonio, TX 78215

REORDER NO. 0064-1080-59
PATENT NO. 6,846,846